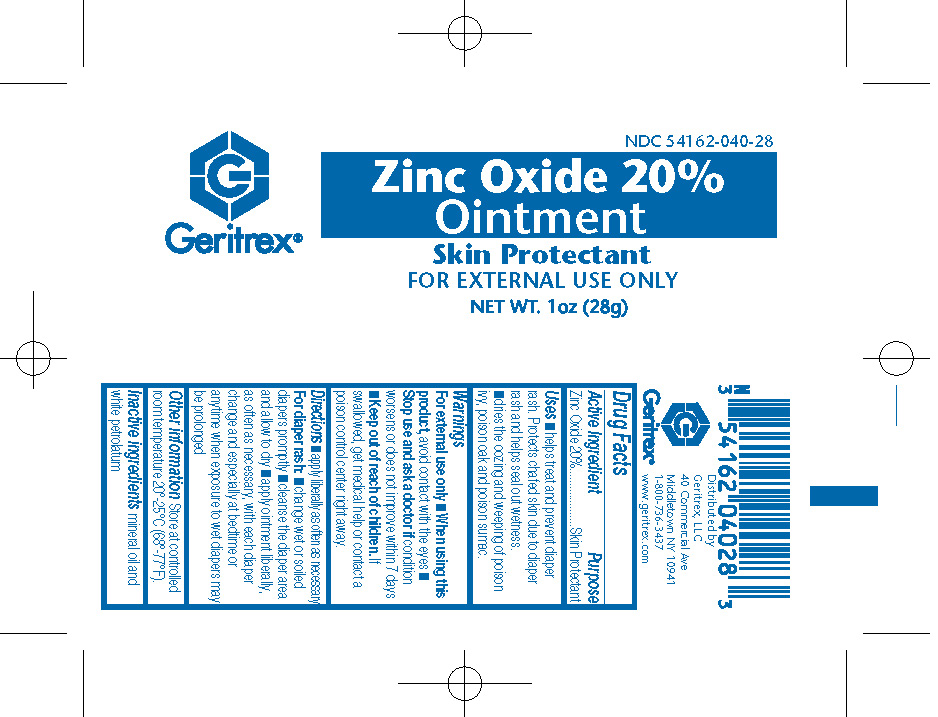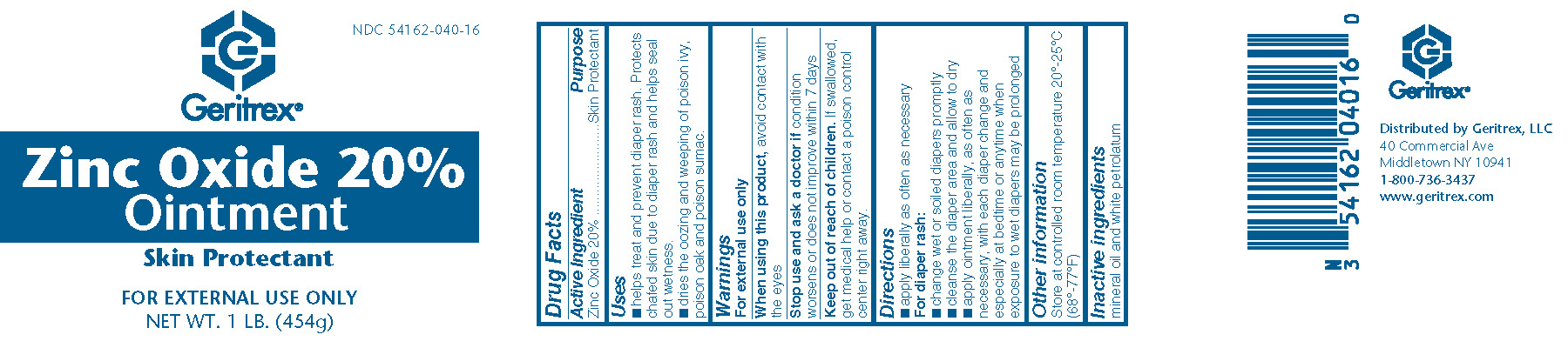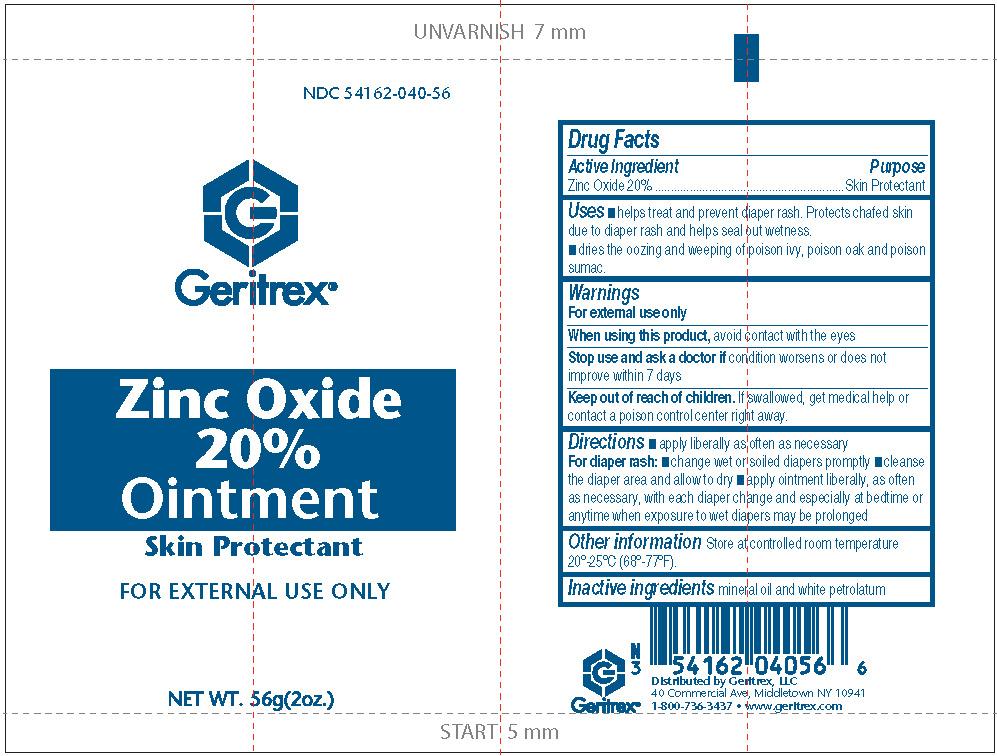 DRUG LABEL: Zinc Oxide 20%
NDC: 54162-040 | Form: OINTMENT
Manufacturer: GERITREX LLC
Category: otc | Type: HUMAN OTC DRUG LABEL
Date: 20180905

ACTIVE INGREDIENTS: ZINC OXIDE .2 g/1 g
INACTIVE INGREDIENTS: MINERAL OIL; PETROLATUM

Zinc Oxide 20% Ointment

Active Ingredient

Zinc Oxide 20%

Purpose

Skin Protectant

Uses

- helps treat and prevent diaper rash. Protects chafed skin due to diaper rash and helps seal out wetness.
- dries the oozing and weeping of, poison ivy, poison oak and poison sumac

Warnings

When using this product avoid contact with the eyes

Stop use and ask a doctor if condition worsens or does not improve within 7 days

Keep out of reach of children.

If swallowed, get medical help or contact a poison control center right away.

Directions

apply liberally as often as necessary

For diaper rash:

- change wet or soiled diapers promptly
- cleanse the diaper area and allow to dry
- apply ointment liberally, as often as necessary, with each diaper change and especially at bedtime or anytime when exposure to wet diapers may be prolonged

Other information

Store at controlled room temperature 20°-25°C (68°-77°F).

Inactive ingredients

mineral oil, petrolatum